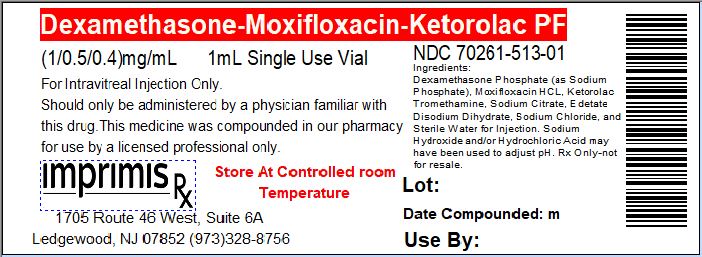 DRUG LABEL: DexMoxiKetor PF
NDC: 70261-513 | Form: INJECTION, SOLUTION
Manufacturer: ImprimisRx NJ
Category: prescription | Type: HUMAN PRESCRIPTION DRUG LABEL
Date: 20180508

ACTIVE INGREDIENTS: MOXIFLOXACIN HYDROCHLORIDE MONOHYDRATE 0.5 mg/1 mL; DEXAMETHASONE SODIUM PHOSPHATE 1 mg/1 mL; KETOROLAC TROMETHAMINE 0.4 mg/1 mL

STORAGE AND HANDLING

Store at 20° to 25° C (68° to 77° F)